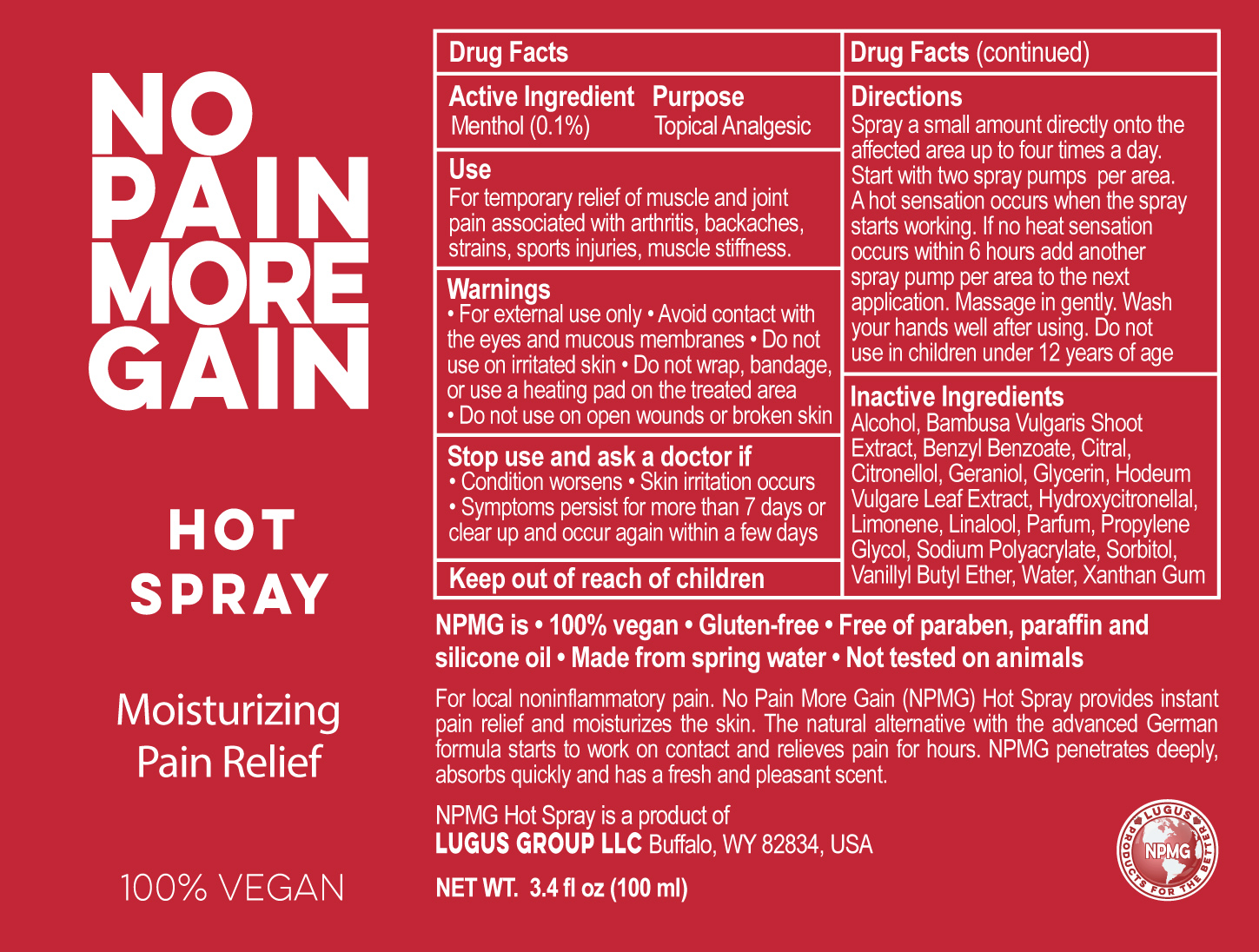 DRUG LABEL: No Pain More Gain
NDC: 69161-003 | Form: SPRAY
Manufacturer: LUGUS GROUP LLC
Category: otc | Type: HUMAN OTC DRUG LABEL
Date: 20191217

ACTIVE INGREDIENTS: MENTHOL 0.1 mg/100 mg
INACTIVE INGREDIENTS: GLYCERIN; BENZYL BENZOATE; .BETA.-CITRONELLOL, (R)-; VANILLYL BUTYL ETHER; LINALOOL, (-)-; ALCOHOL; GERANIOL; HYDROXYCITRONELLAL; HORDEUM VULGARE TOP; SODIUM POLYACRYLATE (2500000 MW); BAMBUSA VULGARIS STEM; XANTHAN GUM; SORBITOL; PROPYLENE GLYCOL; LIMONENE, (+)-; WATER; CITRAL

Active Ingredient

Menthol (0.1%)

Purpose

Topical Analgesic

Use

For temporary relief of muscle and joint pain associated with arthritis, backaches, strains, sports injuries and muscle stiffness

Keep out of reach of children

Stop use and ask a doctor if

• Condition worsens • skin irritation occurs • Symptoms persist for more than 7 days or clear up and occur again within a few days

Inactive Ingredients

Alcohol, Bambusa Vulgaris Shoot Extract, Benzyl Benzoate, Citral, Citronellol, Geraniol, Glycerin, Hordeum Vulgare Leaf Extract, Hydroxycitronellal, Limonene, Linalool, Parfum, Propylene Glycol, Sodium Polyacrylate,Sorbitol, Vanillyl Butyl Ether, Water, Xanthan Gum

Warnings

• For external use only • Avoid contact with the eyes and mucous membranes • Do not use on irritated skin • Do not wrap, bandage, or use a heating pad on the treated area • Do not use on open wounds or broken skin.

INDICATIONS AND USAGE

100% Vegan

No Pain More Gain

Hot Spray

Moisturizing Pain Relief

NPMG is • 100% vegan • Gluten-free • Free of paraben, paraffin and silicone oil • Made from spring water • Not tested on animals

For local noninflammatory pain. No Pain More Gain (NPMG) Hot Spray provides instant pain relief and moisturizes the skin. The natural alternative with the advanced German formula starts to work on contact and relieves pain for hours. NPMG penetrates deeply, absorbs quickly and has a fresh and pleasant scent.

NPMG Hot Spray is a product of

Lugus Group LLC, Buffalo, WY 82834, USA

NET WT 3.4 fl oz (100 ml)

Directions

Spray a small amount directly onto the affected area up to four times a day. Do not use in children under 12 years of age. Wash your hands well after using.